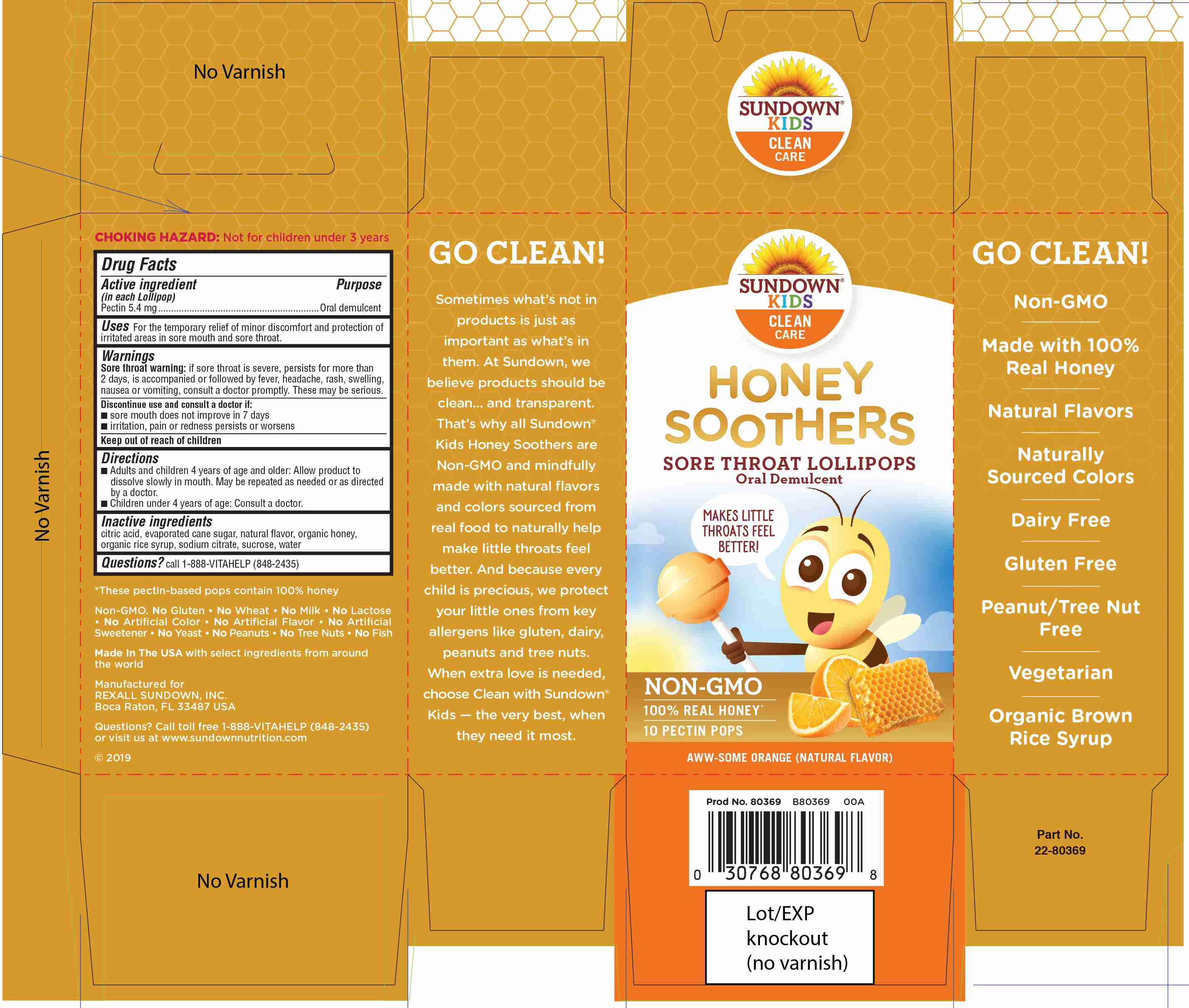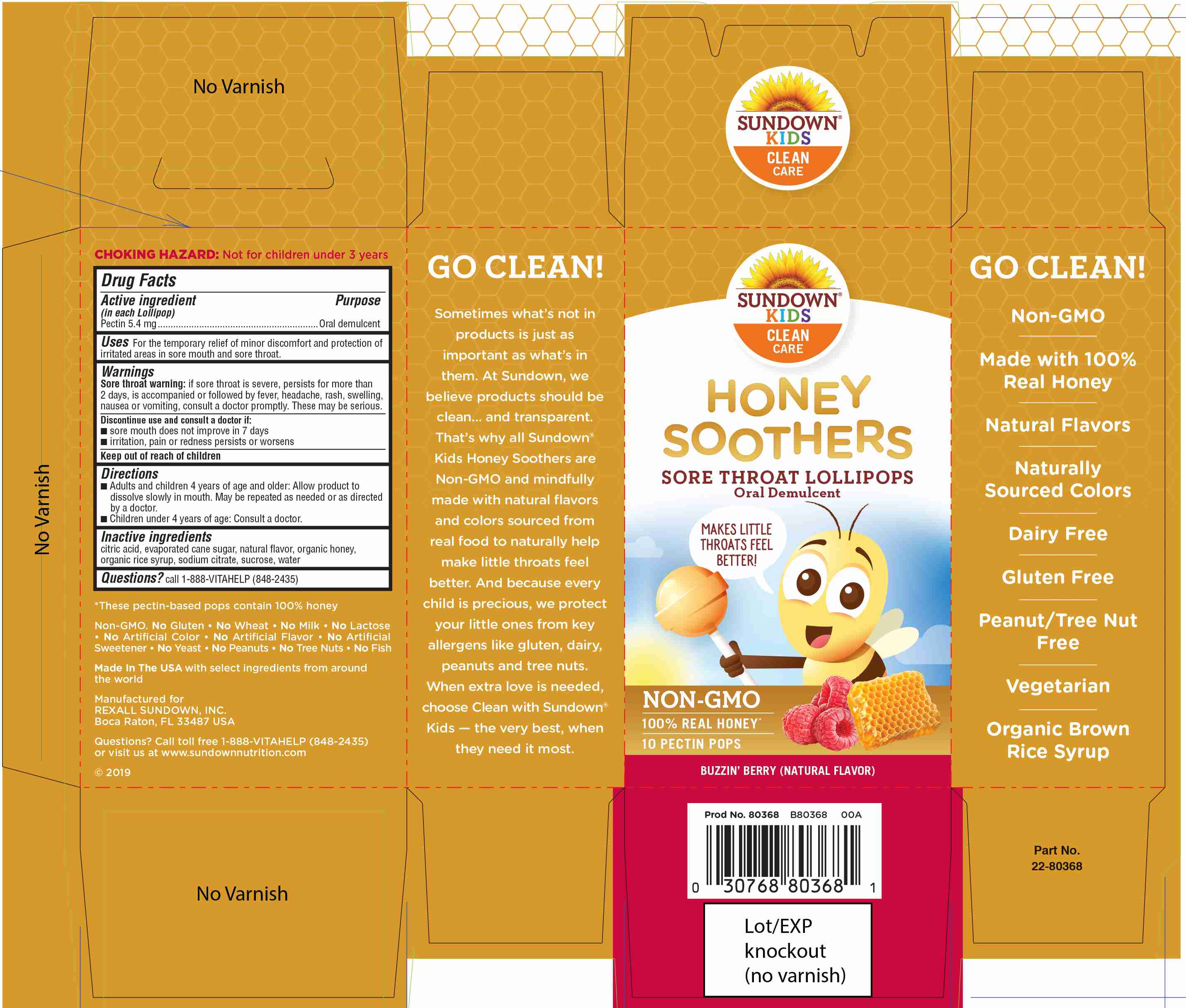 DRUG LABEL: Sundown Honey Soothers Lollipops
NDC: 24737-1902 | Form: LOZENGE
Manufacturer: The Nature's Bounty Company
Category: otc | Type: HUMAN OTC DRUG LABEL
Date: 20181228

ACTIVE INGREDIENTS: PECTIN 0.1 g/100 g
INACTIVE INGREDIENTS: SUCROSE 40 g/100 g; WATER 50 g/100 g; HONEY 9 g/100 g

Active Ingredient

In each Lollipop:

Pectin 5.4 mg..............................................................Oral demulcent

Uses

For the temporary relief of minor discomfort and protection of irritated areas in sore mouth and sore throat.

Uses

For the temporary relief of minor discomfort and protection of
irritated areas in sore mouth and sore throat.

Directions

■ Adults and children 4 years of age and older: Allow product to
dissolve slowly in mouth. May be repeated as needed or as directed
by a doctor.
■ Children under 4 years of age: Consult a doctor.

Sore throat warning:

if sore throat is severe, persists for more than
2 days, is accompanied or followed by fever, headache, rash, swelling,
nausea or vomiting, consult a doctor promptly. These may be serious.
Discontinue use and consult a doctor if:
■ sore mouth does not improve in 7 days
■ irritation, pain or redness persists or worsens
Keep out of reach of children

Sore throat warning:

if sore throat is severe, persists for more than 2 days, is accompanied or followed by fever, headache, rash, swelling, nausea or vomiting, consult a doctor promptly. These may be serious.

Discontinue use and consult a doctor if:

■ sore mouth does not improve in 7 days
■ irritation, pain or redness persists or worsens

Directions

■ Adults and children 4 years of age and older: Allow product to
dissolve slowly in mouth. May be repeated as needed or as directed
by a doctor.
■ Children under 4 years of age: Consult a doctor.

Inactive ingredients

Citric acid, evaporated cane sugar, natural flavor, organic honey,
organic rice syrup, sodium citrate, sucrose, water

Questions?

Call 1-888-VITAHELP (848-2435)